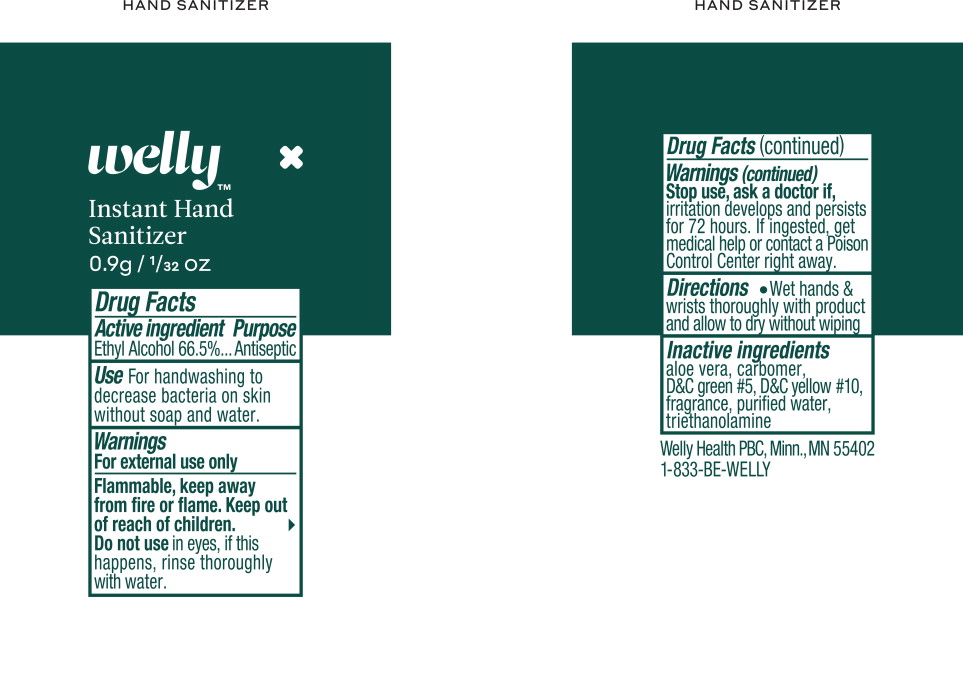 DRUG LABEL: Antiseptic
NDC: 72663-111 | Form: GEL
Manufacturer: Welly Health PCB
Category: otc | Type: HUMAN OTC DRUG LABEL
Date: 20250129

ACTIVE INGREDIENTS: ALCOHOL 666 mg/1 mL
INACTIVE INGREDIENTS: ALOE VERA LEAF; CARBOMER INTERPOLYMER TYPE A (ALLYL SUCROSE CROSSLINKED); D&C GREEN NO. 5; D&C YELLOW NO. 10; WATER; TROLAMINE

Drug Facts

Active ingredient

Ethyl Alcohol 66.5%

Purpose

Antiseptic

Uses

For handwashing to decrease bacteria on skin without soap and water.

Warnings

External use only

Flammable, keep away from fire or flame.

Keep out of reach of children.

Do not use in eyes, if this happens, rinse thoroughly with water.

Stop use, ask a doctor if, irritation develops and persists for 72 hours. If ingested, get medical help or contact a Poison Control Center right away.

Directions

- Wet hands & wrists thoroughly with product and allow to dry without wiping

Inactive ingredients

aloe vera, carbomer, D&C green #5, D&C yellow #10, fragrance, purified water, triethanolamine

Welly Health PBC, Minn., MN 55402

1-833-BE-WELLY

Principal Display Panel - Welly Health Instant Hand Sanitizer Pouch Label

Welly™

Instant Hand
Sanitizer

0.9g/ 1/32 OZ